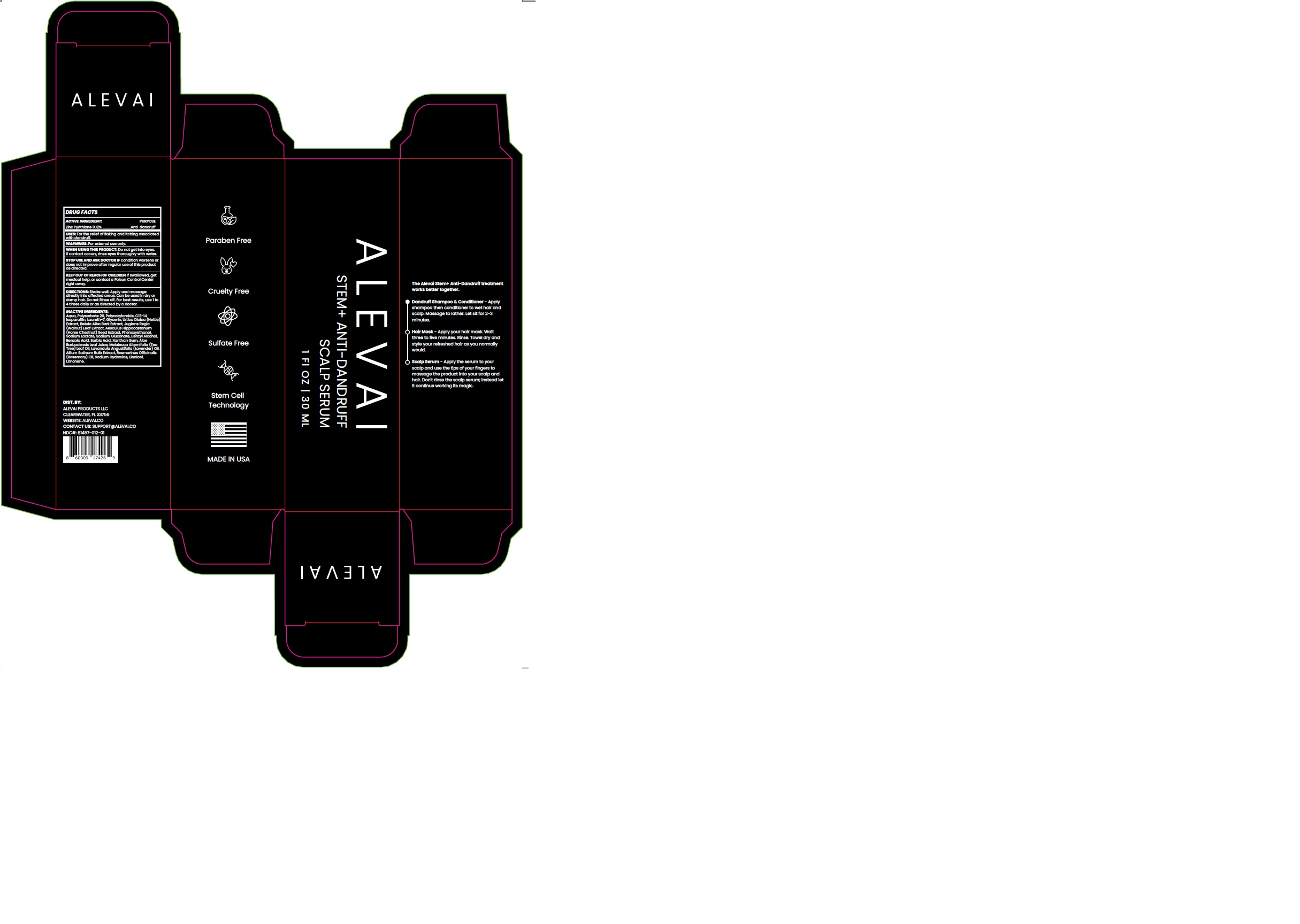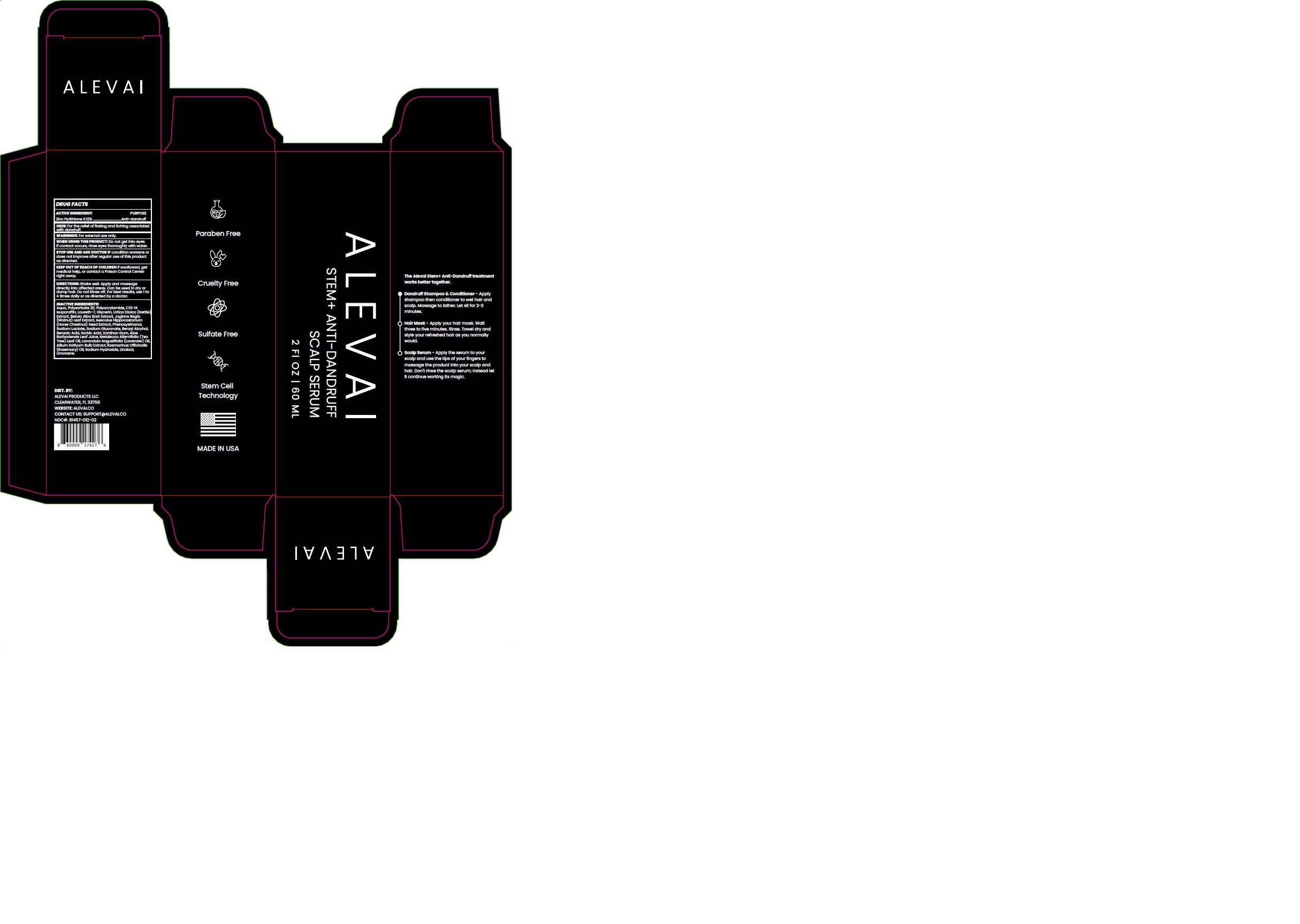 DRUG LABEL: ALEVAI - ANTI DANDRUFF SCALP SERUM
NDC: 81457-012 | Form: CREAM
Manufacturer: ALEVAI PRODUCTS LLC
Category: otc | Type: HUMAN OTC DRUG LABEL
Date: 20241122

ACTIVE INGREDIENTS: PYRITHIONE ZINC 0.12 g/100 mL
INACTIVE INGREDIENTS: SORBIC ACID; URTICA DIOICA LEAF; BETULA PUBESCENS BARK; ALLIUM SATIVUM WHOLE; GLYCERIN; WATER; POLYSORBATE 20; C13-14 ISOPARAFFIN; MELALEUCA ALTERNIFOLIA LEAF; LIMONENE, (+)-; PHENOXYETHANOL; ROSEMARY OIL; LINALOOL, (+/-)-; ALOE VERA LEAF; HORSE CHESTNUT; SODIUM LACTATE; LAURETH-7; XANTHAN GUM; SODIUM HYDROXIDE; SODIUM GLUCONATE; BENZYL ALCOHOL; BENZOIC ACID; LAVENDER OIL; JUGLANS REGIA LEAF

81457-012-01
81457-012-02

ACTIVE INGREDIENT

Zinc Pyrithione 0.12%

PURPOSE

Anti-dandruff

USES:

For the relief of flaking and itching associated with dandruff.

WARNINGS

For external use only.

WHEN USING

Do not get into eyes. If contact occurs, rinse eyes thoroughly with water.

STOP USE AND ASK DOCTOR IF

condition worsens or does not improve after regular use of this product as directed.

KEEP OUT OF REACH OF CHILDREN

If swallowed, get medical help, or contact a Poison Control Center right away.

DIRECTIONS:

Shake well. Apply and massage directly into affected areas. Can be used in dry or damp hair. Do not Rinse off. For best results, use 1 to 4 times daily or as directed by a doctor.

INACTIVE INGREDIENT

Aqua, Polysorbate 20, Polyacrylamide, C13-14 Isoparaffin, Laureth-7, Glycerin, Urtica Dioica (Nettle) Extract, Betula Alba Bark Extract, Juglans Regia (Walnut) Leaf Extract, Aesculus Hippocastanum (Horse Chestnut) Seed Extract, Phenoxyethanol, Sodium Lactate, Sodium Gluconate, Benzyl Alcohol, Benzoic Acid, Sorbic Acid, Xanthan Gum, Aloe Barbadensis Leaf Juice, Melaleuca Alternifolia (Tea Tree) Leaf Oil, Lavandula Angustifolia (Lavender) Oil, Allium Sativum Bulb Extract, Rosmarinus Officinalis (Rosemary) Oil, Sodium Hydroxide, Linalool, Limonene.